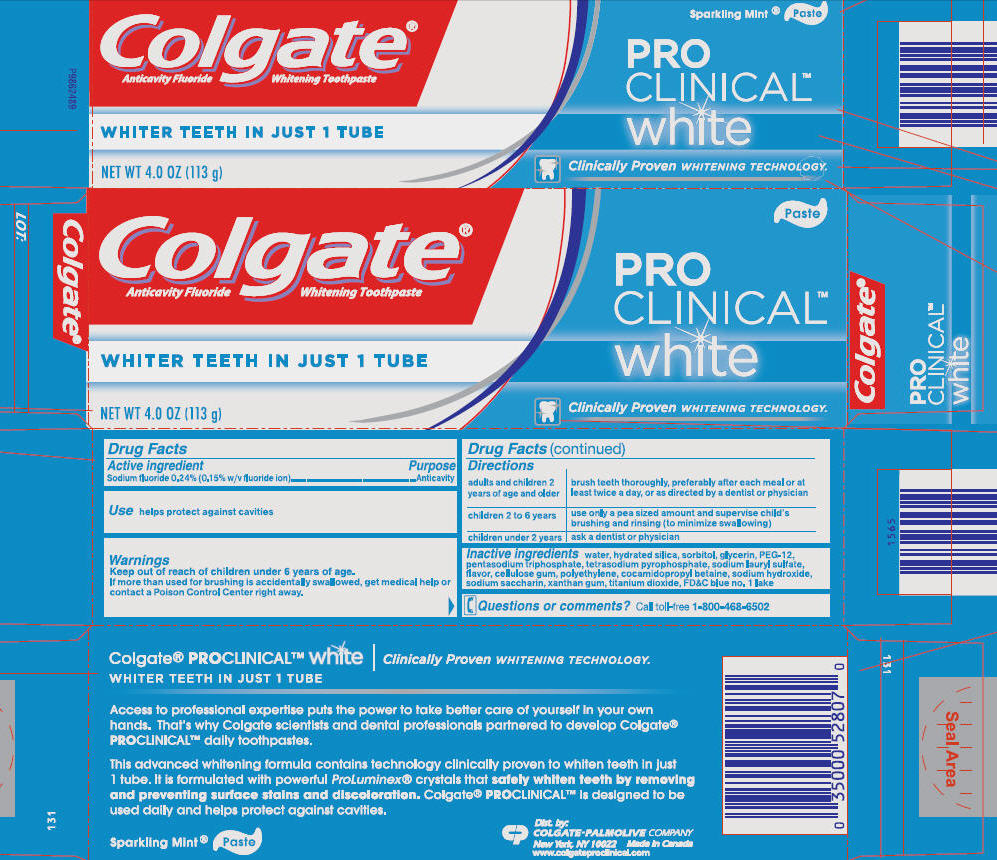 DRUG LABEL: COLGATE PROCLINICAL - Sparkling Mint
NDC: 51442-543 | Form: PASTE, DENTIFRICE
Manufacturer: Colgate-Palmolive Canada
Category: otc | Type: HUMAN OTC DRUG LABEL
Date: 20101216

ACTIVE INGREDIENTS: Sodium Fluoride 2.4 mg/1 g
INACTIVE INGREDIENTS: Water; Hydrated Silica; Sorbitol; Glycerin; Polyethylene Glycol 600; Sodium Tripolyphosphate; Sodium Pyrophosphate; Sodium Lauryl Sulfate; Carboxymethylcellulose Sodium; Cocamidopropyl Betaine; Sodium Hydroxide; Saccharin Sodium; Xanthan Gum; Titanium Dioxide; FD&C Blue No. 1

Colgate®
FLUORIDE TOOTHPASTE

Drug Facts

Active ingredients

Sodium fluoride 0.24% (0.15% w/v fluoride ion)

Purpose

Anticavity

Uses

helps protect against cavities

Warnings

Keep out of reach of children under 6 years of age. If more than used for brushing is accidentally swallowed, get medical help or contact a Poison Control Center right away.

Directions

adults and children 2 years of age and older | brush teeth thoroughly, preferably after each meal or at least twice a day, or as directed by a dentist or physician
children 2 to 6 years | use only a pea sized amount and supervise child's brushing and rinsing (to minimize swallowing)
children under 2 years | ask a dentist or physician

Inactive ingredients

water, hydrated silica, sorbitol, glycerin, PEG-12, pentasodium triphosphate, tetrasodium pyrophosphate, sodium lauryl sulfate, flavor, cellulose gum, polyethylene, cocoamidopropyl betaine, sodium hydroxide, sodium saccharin, xanthan gum, titanium dioxide, FD&C blue no. 1

Questions or comments?

Call toll free 1-800-468-6502

Dist. by:
COLGATE-PALMOLIVE COMPANY
New York, NY 10022
Made in Canada
www.colgateproclinical.com

PRINCIPAL DISPLAY PANEL - 113 g Carton

Colgate®
Anticavity Fluoride Whitening Toothpaste

Paste

PRO
CLINICAL™
white

WHITER TEETH IN JUST 1 TUBE

NET WT 4.0 OZ (113 g)

Clinically Proven WHITENING TECHNOLOGY.